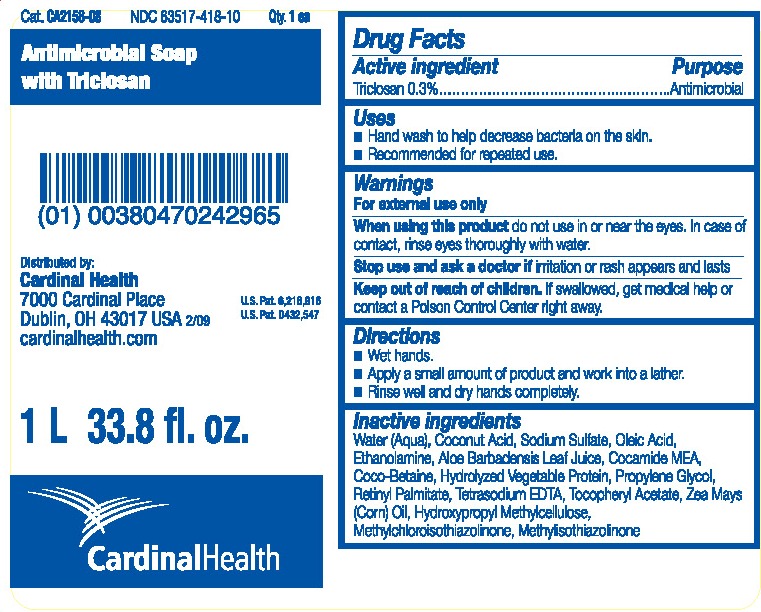 DRUG LABEL: Cardinal Health Antimicrobial Soap with Triclosan
NDC: 63517-418 | Form: LIQUID
Manufacturer: Cardinal Health
Category: otc | Type: HUMAN OTC DRUG LABEL
Date: 20110314

ACTIVE INGREDIENTS: TRICLOSAN 0.003 mL/1 mL
INACTIVE INGREDIENTS: WATER; ALOE VERA LEAF; COCONUT ACID; SODIUM SULFATE; OLEIC ACID; MONOETHANOLAMINE; COCO MONOETHANOLAMIDE; Propylene glycol; VITAMIN A PALMITATE; EDETATE SODIUM; ALPHA-TOCOPHEROL ACETATE; Corn oil; HYPROMELLOSES; METHYLCHLOROISOTHIAZOLINONE; METHYLISOTHIAZOLINONE

PACKAGE LABEL

Cardinal Health Antimicrobial Soap with Triclosan

Directions:

- Wet hands
- Apply a small amount of product and work into a lather
- Rinse well and dry hands completely

DOSAGE AND ADMINISTRATION

Apply approx. 1.5 mL

PURPOSE

Antimicrobial

Keep out of reach of children.

Warnings
For external use only
When using this product do not use in or near the eyes. In case of contact, rinse eyes thoroughly with water.
Stop use and ask a doctor if irritation or rash appears and lasts
Keep out of reach of children. If swallowed, get medical help or contact a Poison Control Center right away.

Active ingredient Triclosan 0.3%

INACTIVE INGREDIENT

Inactive Ingredients Water (Aqua), Coconut Acid, Sodium Sulfate, Oleic Acid, Ethanolamine, Aloe Barbadensis Leaf Juice, Cocamide MEA, Coco-Betaine, Hydrolyzed Vegetable Protein, Propylene Glycol, Retinyl Palmitate, Tetrasodium EDTA, Tocopheryl Acetate, Zea Mays (Corn) Oil, Hydroxypropyl Methylcellulose, Methylchloroisothiazolinone, Methylisothiazolinone